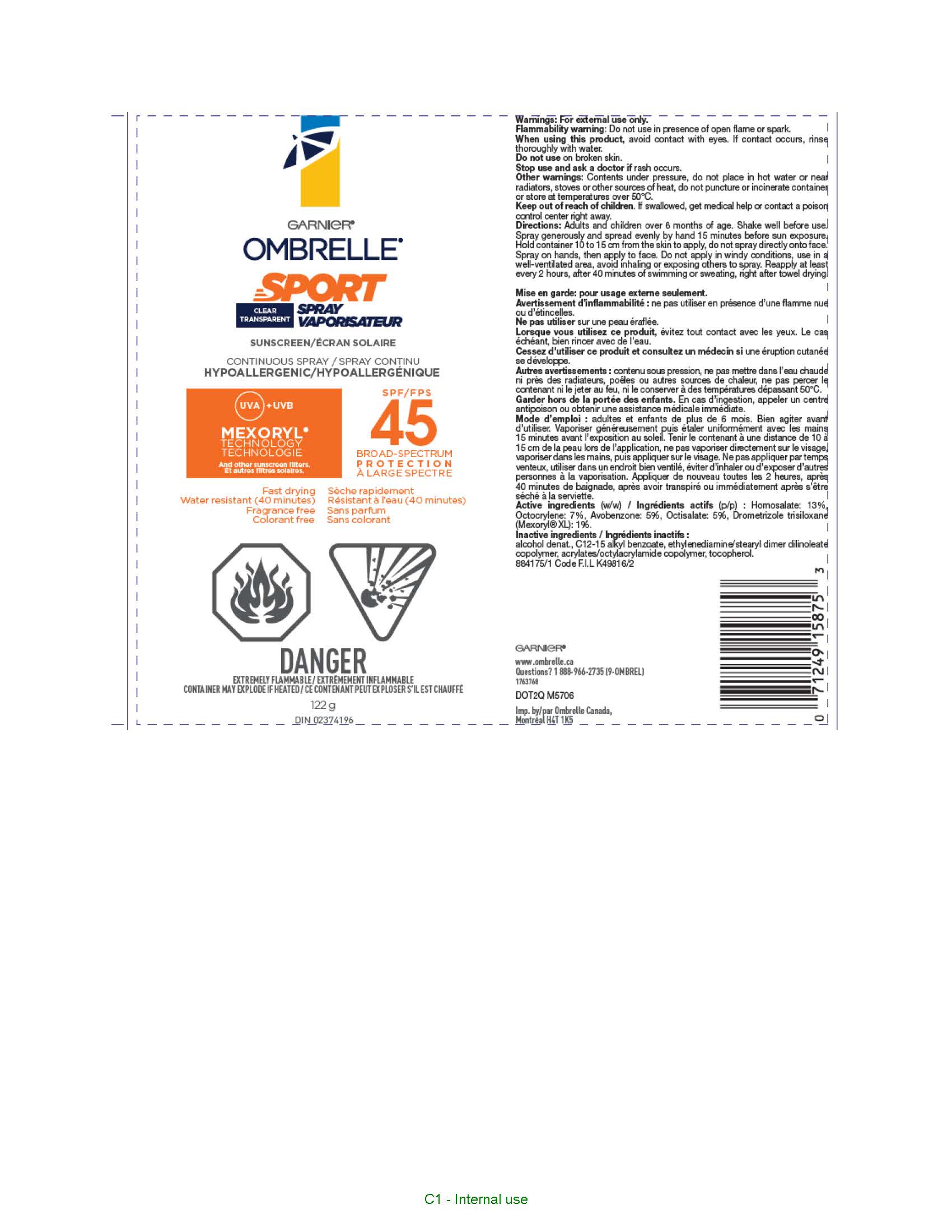 DRUG LABEL: Garnier Ombrelle Clear Sport 45 Water Resistant 40 Minutes
NDC: 49967-753 | Form: SPRAY
Manufacturer: L'OREAL USA PRODUCTS INC
Category: otc | Type: HUMAN OTC DRUG LABEL
Date: 20260107

ACTIVE INGREDIENTS: AVOBENZONE 50 mg/1 mL; DROMETRIZOLE TRISILOXANE 10 mg/1 mL; HOMOSALATE 130 mg/1 mL; OCTISALATE 50 mg/1 mL; OCTOCRYLENE 70 mg/1 mL
INACTIVE INGREDIENTS: ALCOHOL; ALKYL (C12-15) BENZOATE; TOCOPHEROL

Drug Facts

Active ingredients

Avobenzone 5%

Drometrizole trisiloxane 1%

Homosalate 13%

Octisalate 5%

Octocrylene 7%

Warnings

For external use only. Flammability Warning. Do not use in presence of open flame or spark. When using this product avoid contact witheyes. If contact occurs, rinse thoroughlly with water. Do not use on broken skin. Stop use and ask a doctor if rash occurs. Other warnings. Contents under pressure, do not place in hot water or near radiator, stoves or other sources of heat, do not puncture or incinerate container or store at temperatures over 50oC. Keep out of reach of children. If swallowed get medical help or contact a poison control center right away.

Directions

Adults and children over 6 months of age. Shake well before use. Spray generously and spread evenly by hand 15 minutes before sun exposure. Hold container 10 to 15 cm from the skin to apply, do not spray directly onto face. Spray on hand then apply to face. Do not apply in windy conditions and use in a well ventilated area, avoid inhaling or exposing others to spray. Reapply at least every 2 hours, after 80 minutes of swimming or sweating, right after towel drying.

Others

alcohol denat., c12-15 alkyl benzoate, ethylenediamine/stearyl dimer dilinoleate copolymer, acrylates/octylacrylamide copolymer, tocopherol